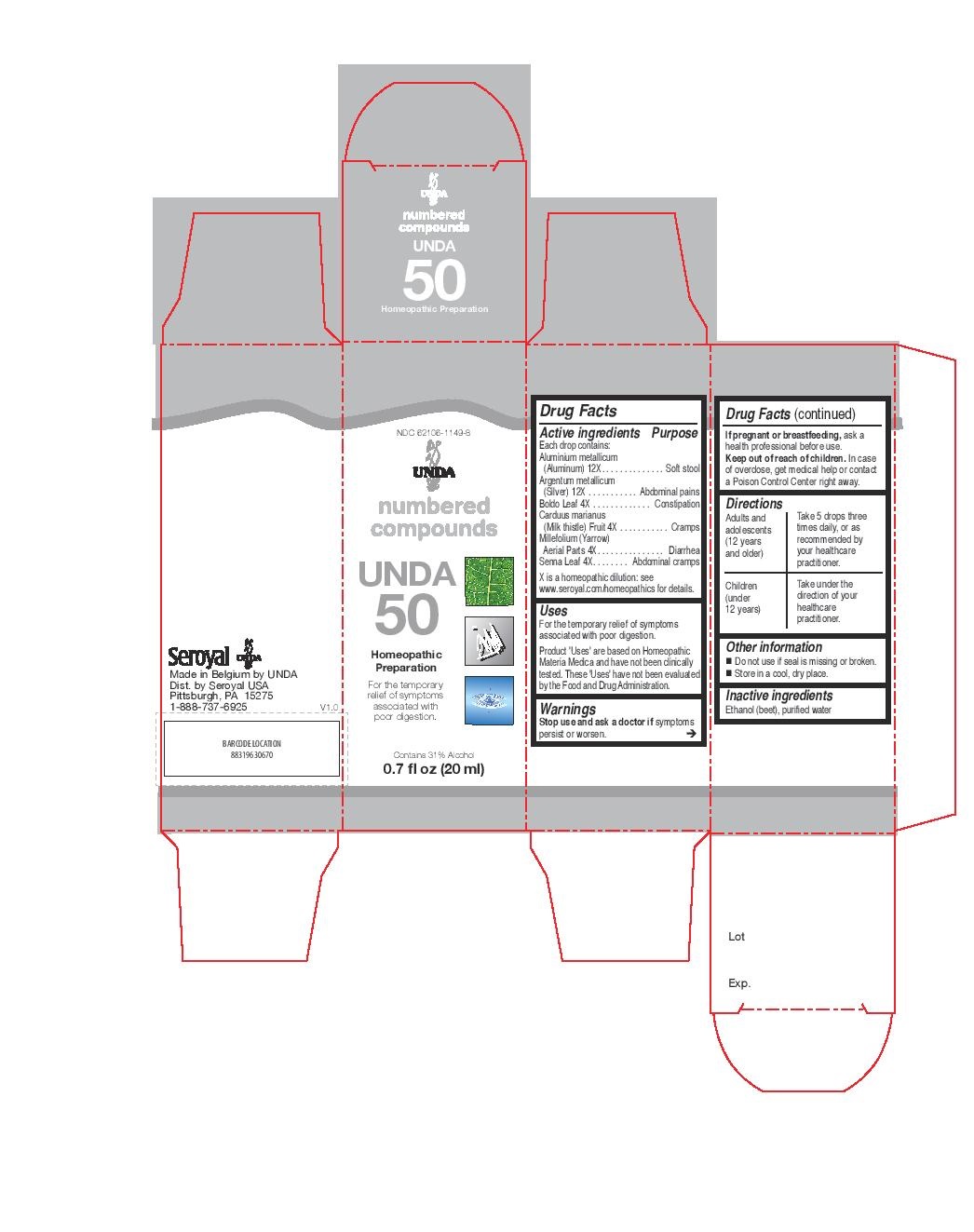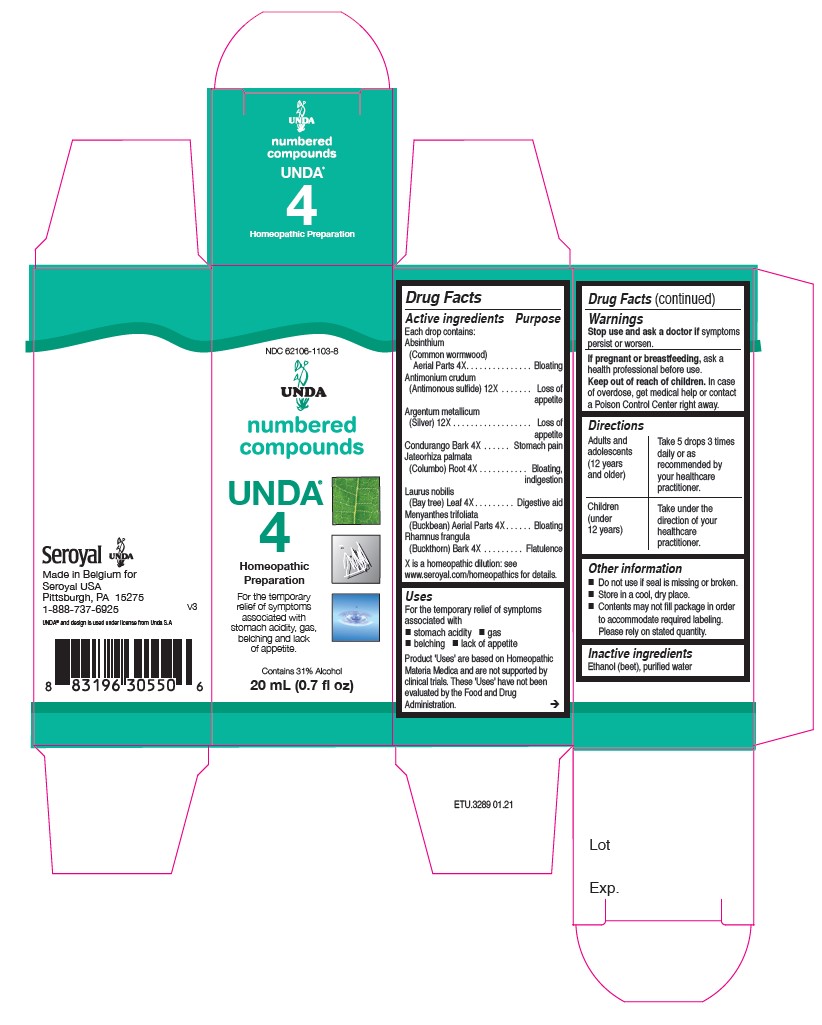 DRUG LABEL: UNDA 50
NDC: 62106-1149 | Form: LIQUID
Manufacturer: Seroyal USA
Category: homeopathic | Type: HUMAN OTC DRUG LABEL
Date: 20210715

ACTIVE INGREDIENTS: PEUMUS BOLDUS LEAF 4 [hp_X]/20 mL; SENNA LEAF 4 [hp_X]/20 mL; SILYBUM MARIANUM SEED 4 [hp_X]/20 mL; ACHILLEA MILLEFOLIUM 4 [hp_X]/20 mL; ALUMINUM 12 [hp_X]/20 mL; SILVER 12 [hp_X]/20 mL
INACTIVE INGREDIENTS: ALCOHOL; WATER

UNDA numbers

Active ingredients
Each drop contains:
Absinthium (Common wormwood) Aerial Parts 4X
Antimonium crudum (Antimonous sulfide) 12X
Argentum metallicum (Silver) 12X
Condurango Bark 4X
Jateorhiza palmata (Columbo) Root 4X
Laurus nobilis (Bay tree) Leaf 4X
Menyanthes trifoliata (Buckbean) Aerial Parts 4X
Rhamnus frangula (Buckthorn) Bark 4X

Uses
For the temporary relief of symptoms associated with stomach
acidity, gas, belching and lack of appetite.

Warnings
Stop use and ask a doctor if symptoms
persist or worsen.
If pregnant or breastfeeding, ask a
health professional before use.
Keep out of reach of children. In case
of overdose, get medical help or contact
a Poison Control Center right away.

PREGNANCY OR BREAST FEEDING

If pregnant or breastfeeding, ask a health professional before use.

Keep out of reach of children.

OVERDOSAGE

In case of overdose, get medical help or contact a Poison Control Center right away.

Stop use and ask a doctor if symptoms persist or worsen.

Inactive Ingredients:

Ethanol (beet),
purified water

Directions

Adults and adolescents (12 years and older)

Take 5 drops three times daily or as recommended by your healthcare practitioner.

Children (under 12 years)

Take under the direction of your healthcare practitioner.

Uses

For the temporary relief of symptoms associated with
stomach acidity, gas, belching and lack of appetite.

Directions

Adults and adolescents (12 years and older)

Take 5 drops three times daily or as recommended by your healthcare practitioner.

Children (under 12 years)

Take under the direction of your healthcare practitioner.

Active ingredients
Each drop contains:
Aluminium metallicum (Aluminum) 12X
Argentum metallicum (Silver) 12X
Boldo Leaf 4X
Carduus marianus (Milk thistle) Fruit 4X
Millefolium (Yarrow) Aerial Parts 4X
Senna Leaf 4X

Uses

For the temporary relief of symptoms
associated with poor digestion.

Warnings

Stop use and ask a doctor if symptomspersist or worsen

If you are pregnant or breastfeeding, ask a healthcare practitioner before use.
Keep out of reach of children.
In case of overdose, get medical help or contact a Poison Control Center right away.

PREGNANCY OR BREAST FEEDING

If you are pregnant or breastfeeding, ask a healthcare practitioner before use.

Keep out of reach of children.

OVERDOSAGE

In case of overdose, get medical help or contact a Poison Control Center right away.

Inactive Ingredients:

Ethanol (beet),
purified water

Directions
Adults and Children (12 years and older)

Take 5 drops three times daily or as recommended by your healthcare practitioner.

Children (under 12 years)

Takeunder the direction of your healthcare practitioner.

Uses
For the temporary relief of symptoms associated with poor digestion.

Directions
Adults and Children (12 years and older)

Take 5 drops three times daily or as recommended by your healthcare practitioner.

Children (under 12 years)

Take under the direction of your healthcare practitioner.

Other information
Do not use if seal is missing or broken.
Store in a cool, dry place.

Contents may not fill package in order
to accommodate required labeling.
Please rely on stated quantity.

PACKAGE LABEL

NDC 62106-1149-8

UNDA

numbered compounds

UNDA 50

Homeopathic Preparation

For the temporary relief of symptoms associated with poor digestion.

Contains 31% Alcohol
0.7 fl oz (20 ml)

PACKAGE LABEL

NDC 62106-1103-8

UNDA

numbered compounds

UNDA 4

Homeopathic Preparation

For the temporary
relief of symptoms
associated with
stomach acidity, gas,
belching and lack
of appetite.

Contains 31% Alcohol
0.7 fl oz (20 ml)